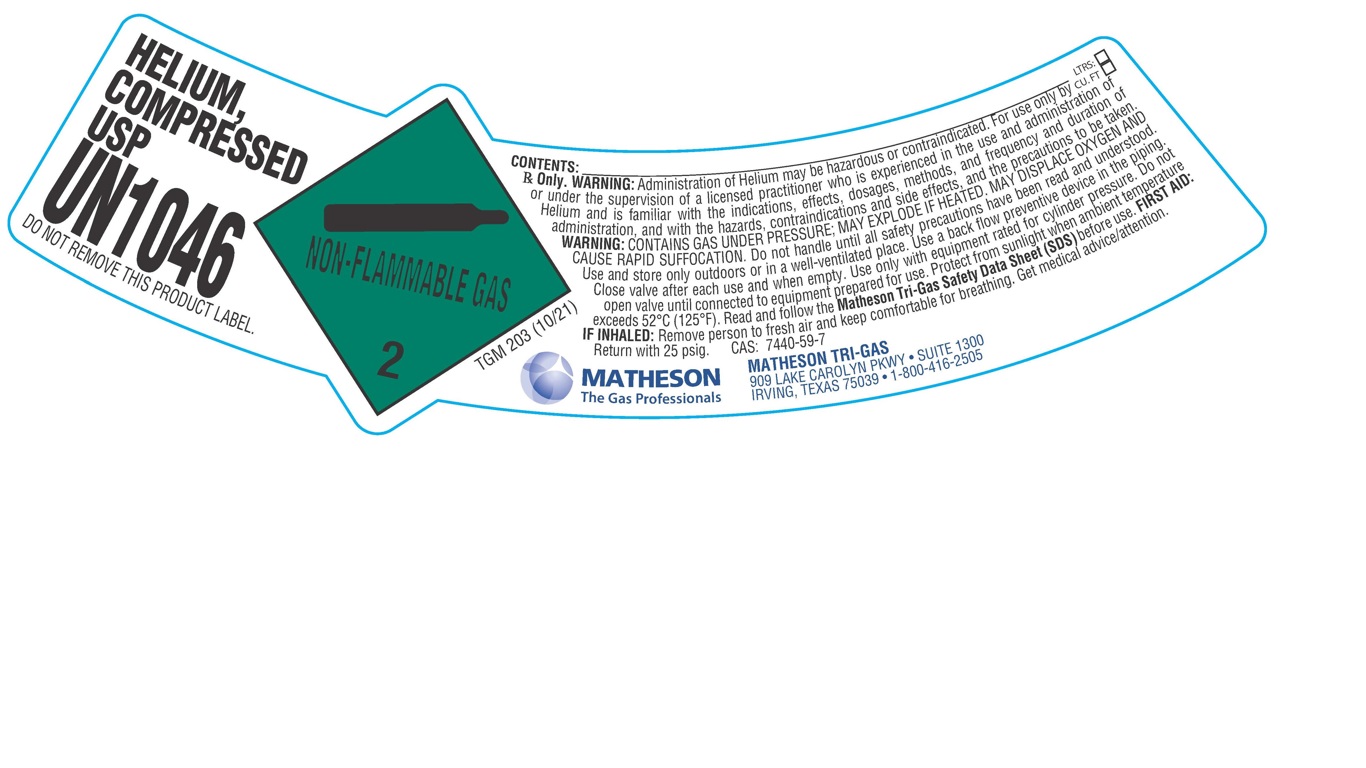 DRUG LABEL: Helium
NDC: 55037-501 | Form: GAS
Manufacturer: Matheson Tri-Gas, Inc.
Category: prescription | Type: HUMAN PRESCRIPTION DRUG LABEL
Date: 20251202

ACTIVE INGREDIENTS: HELIUM 992 mL/1 L

Helium

PACKAGE LABEL

HELIUM, COMPRESSED USP

UN1046

DO NOT REMOVE THIS PRODUCT LABEL.

CONTENTS: LTRS: CU.FT:

Rx Only. WARNING: Administration of Helium may be hazardous or contraindicated. For use only by or under the supervision of a licensed practitioner who is experienced in the use and administration of Helium and is familiar with the indications, effects, dosages, methods, and frequency and duration of administration, and with the hazards, contraindications and side effects, and the precautions to be taken. WARNING: CONTAINS GAS UNDER PRESSURE; MAY EXPLODE IF HEATED. MAY DISPLACE OXYGEN AND CAUSE RAPID SUFFOCATION. Do not handle until all safety precautions have been read and understood. Use and store only outdoors or in a well-ventilated place. Use a back flow preventive device in the piping. Close valve after each use and when empty. Use only with equipment rated for cylinder pressure. Do not open valve until connected to equipment prepared for use. Protect from sunlight when ambient temperature exceeds 52 C (125 F). Read and follow the Matheson Tri-Gas Safety Data Sheet (SDS) before use. FIRST AID: IF INHALED: Remove person to fresh air and keep comfortable for breathing. Get medical advice/attention. Return with 25 psig. CAS: 7440-59-7

MATHESON The Gas Professionals

MATHESON TRI-GAS

909 LAKE CAROLYN PKWY. SUITE 1300

IRVING, TEXAS 75039 . 1-800-416-2505